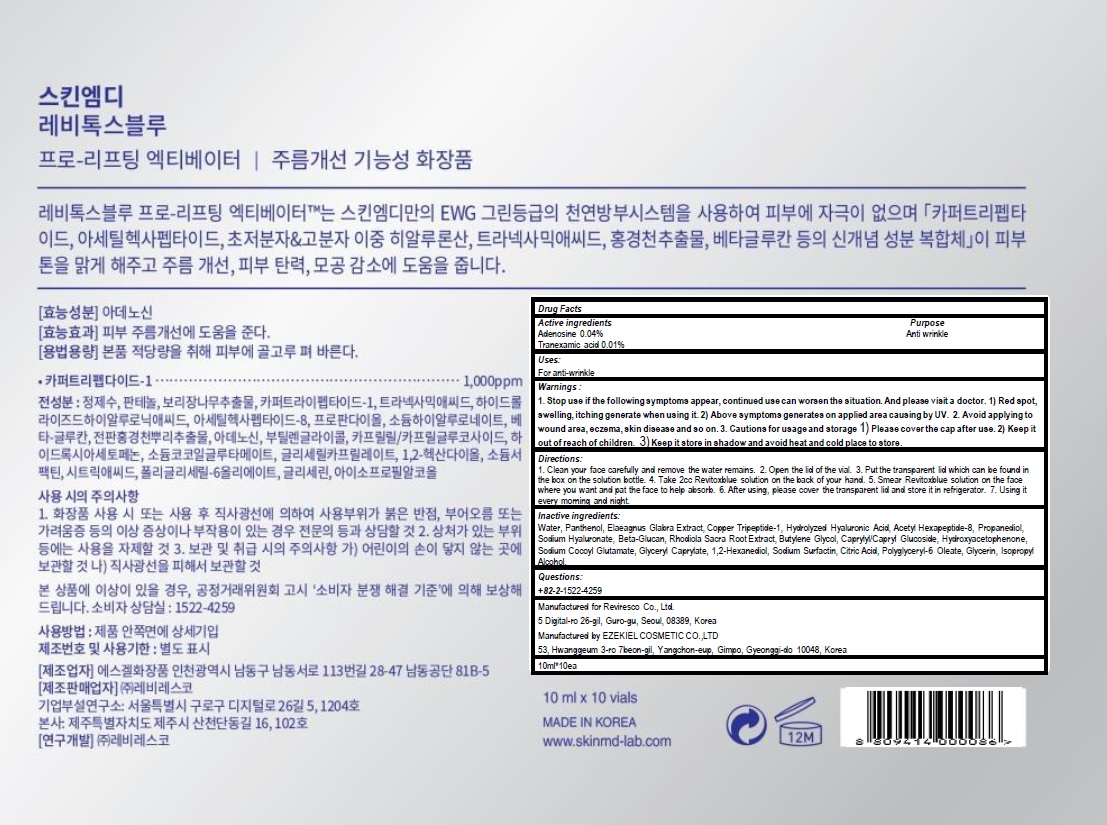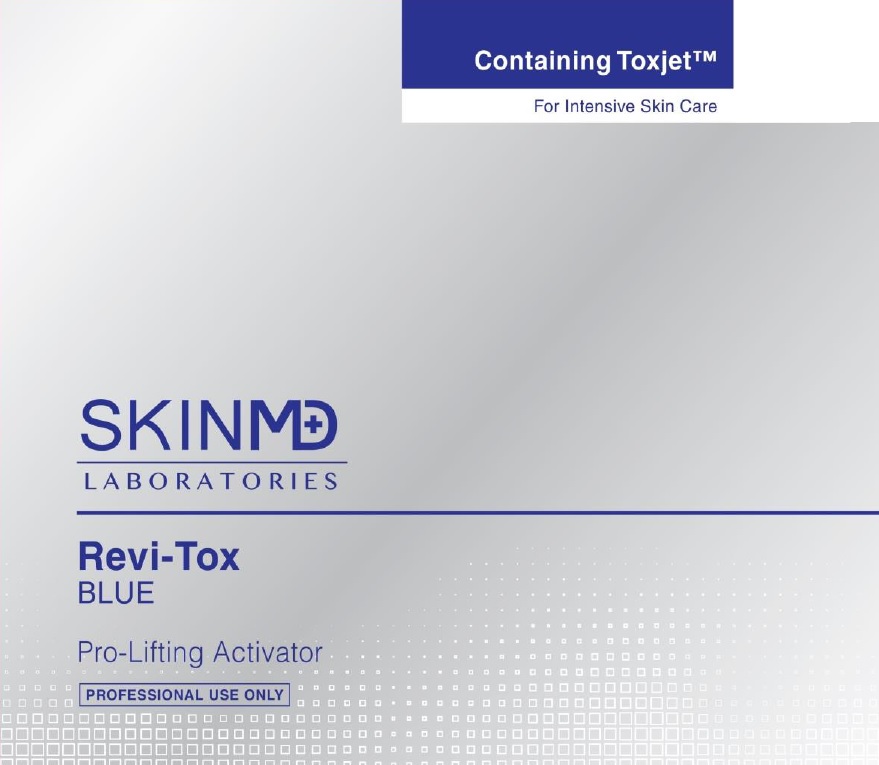 DRUG LABEL: SKINMD LABORATORIES ReviTox blue
NDC: 71974-040 | Form: LIQUID
Manufacturer: Reviresco Co., Ltd.
Category: otc | Type: HUMAN OTC DRUG LABEL
Date: 20181128

ACTIVE INGREDIENTS: Adenosine 0.004 g/10 mL; Tranexamic acid 0.001 g/10 mL
INACTIVE INGREDIENTS: Water; Panthenol

ACTIVE INGREDIENT

Active ingredients: Adenosine 0.04%, Tranexamic acid 0.01%

INACTIVE INGREDIENT

Inactive ingredients:

Water, Panthenol, Elaeagnus Glabra Extract, Copper Tripeptide-1, Hydrolyzed Hyaluronic Acid, Acetyl Hexapeptide-8, Propanediol, Sodium Hyaluronate, Beta-Glucan, Rhodiola Sacra Root Extract, Butylene Glycol, Caprylyl/Capryl Glucoside, Hydroxyacetophenone, Sodium Cocoyl Glutamate, Glyceryl Caprylate, 1,2-Hexanediol, Sodium Surfactin, Citric Acid, Polyglyceryl-6 Oleate, Glycerin, Isopropyl Alcohol

PURPOSE

Purpose: Anti wrinkle

WARNINGS

1. Stop use if the following symptoms appear, continued use can worsen the situation. And please visit a doctor.
- Red spot, swelling, itching generate when using it.
- Above symptoms generates on applied area causing by UV.
2. Avoid applying to wound area, eczema, skin disease and so on.
3. Cautions for usage and storage
- Please cover the cap after use.
- Keep it out of reach of children.
- Keep it store in shadow and avoid heat and cold place to store.

KEEP OUT OF REACH OF CHILDREN

Keep it out of reach of children

Uses

Uses: For anti-wrinkle

Directions

1. Clean your face carefully and remove the water remains.
2. Open the lid of the vial.
3. Put the transparent lid which can be found in the box on the solution bottle.
4. Take 2cc Revitoxblue solution on the back of your hand.
5. Smear Revitoxblue solution on the face where you want and pat the face to help absorb.
6. After using, please cover the transparent lid and store it in refrigerator.
7. Using it every morning and night.

Questions

+82-2-1522-4259

PACKAGE LABEL

Caton Image 1

PACKAGE LABEL

Carton Image 2